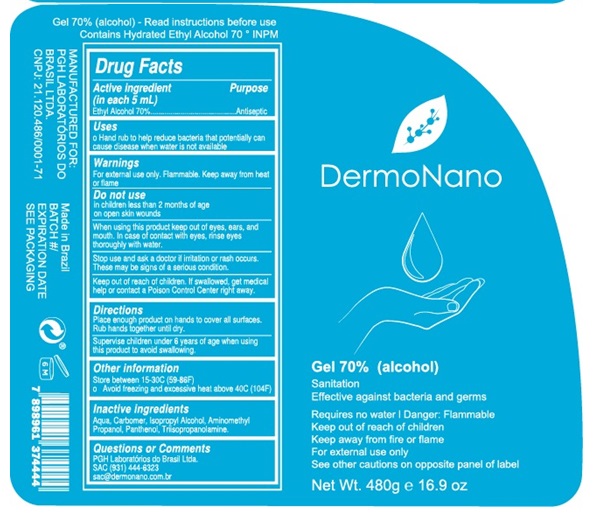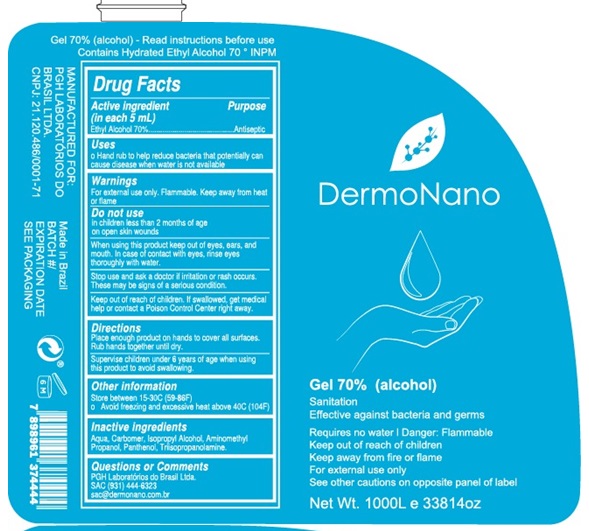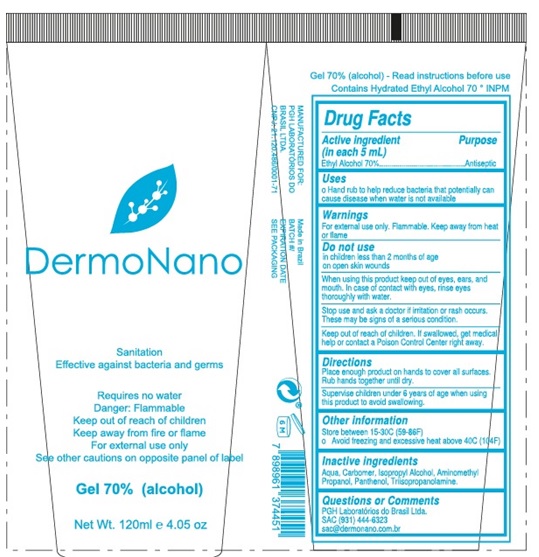 DRUG LABEL: DermoNano
NDC: 75751-070 | Form: GEL
Manufacturer: PGH LABORATORIOS DO BRASIL LTDA.
Category: otc | Type: HUMAN OTC DRUG LABEL
Date: 20200512

ACTIVE INGREDIENTS: ALCOHOL 70 mL/100 mL
INACTIVE INGREDIENTS: WATER; CARBOMER HOMOPOLYMER, UNSPECIFIED TYPE; ISOPROPYL ALCOHOL; AMINOMETHYLPROPANOL; PANTHENOL; TRIISOPROPANOLAMINE

Active Ingredient

Ethyl Alcohol 70%

Purpose

Antiseptic

Use

Hand rub to help reduce bacteria that potentially can cause disease when water is not available.

Warnings

For external use only. Flammable. Keep away from heat or flame

Do not use

- in children less than 2 months of age
- on open skin wounds

When using this product

Keep out of eyes, ears, and mouth. In case of contact with eyes, rinse eyes thoroughly with water.

Stop use and ask a doctor if

Irritation or rash occurs. These may be signs of a serious condition.

Keep out of reach of children.

If swallowed, get medical help or contact a Poison Control Center right away.

Directions

- Place enough product on hands to cover all surfaces. Rub hands together until dry.
- Supervise children under 6 years of age when using this product to avoid swallowing.

Other information

- Store between 15-30C (59-86F)
- Avoid freezing and excessive heat above 40C (104F)

Inactive ingredients

Aqua, Carbomer, Isopropyl Alcohol, Aminomethyl Propanol, Panthenol, Triisopropanolamine

Questions or Comments

PGH Laboratorios do Brasil Ltda.

SAC (931) 444-6323

sac@dermonano.com.br

Principal Display Panel

NDC: 75751-070-04

Gel 70% (alcohol) - Read Instructions before use contains Hydrated Ethyl Alcohol 70 INPM

Gel 70% (alcohol)

Sanitation Effective against bacteria and germs

Requires no water

Danger: Flammable

Keep out of reach of children

Keep away from fire or flame

For external use only

See other cautions on opposite panel of label

Net Wt. 120g e 4.2 oz

NDC: 75751-070-16

Gel 70% (alcohol) - Read Instructions before use contains Hydrated Ethyl Alcohol 70 INPM

Gel 70% (alcohol)

Sanitation Effective against bacteria and germs

Requires no water

Danger: Flammable

Keep out of reach of children

Keep away from fire or flame

For external use only

See other cautions on opposite panel of label

Gel 70% (alcohol)

Net Wt. 480g e 16.9 oz

NDC: 75751-070-26

Gel 70% (alcohol) - Read Instructions before use contains Hydrated Ethyl Alcohol 70 INPM

Gel 70% (alcohol)

Sanitation Effective against bacteria and germs

Requires no water

Danger: Flammable

Keep out of reach of children

Keep away from fire or flame

For external use only

See other cautions on opposite panel of label

Gel 70% (alcohol)

Net Wt. 1000L e 33814oz